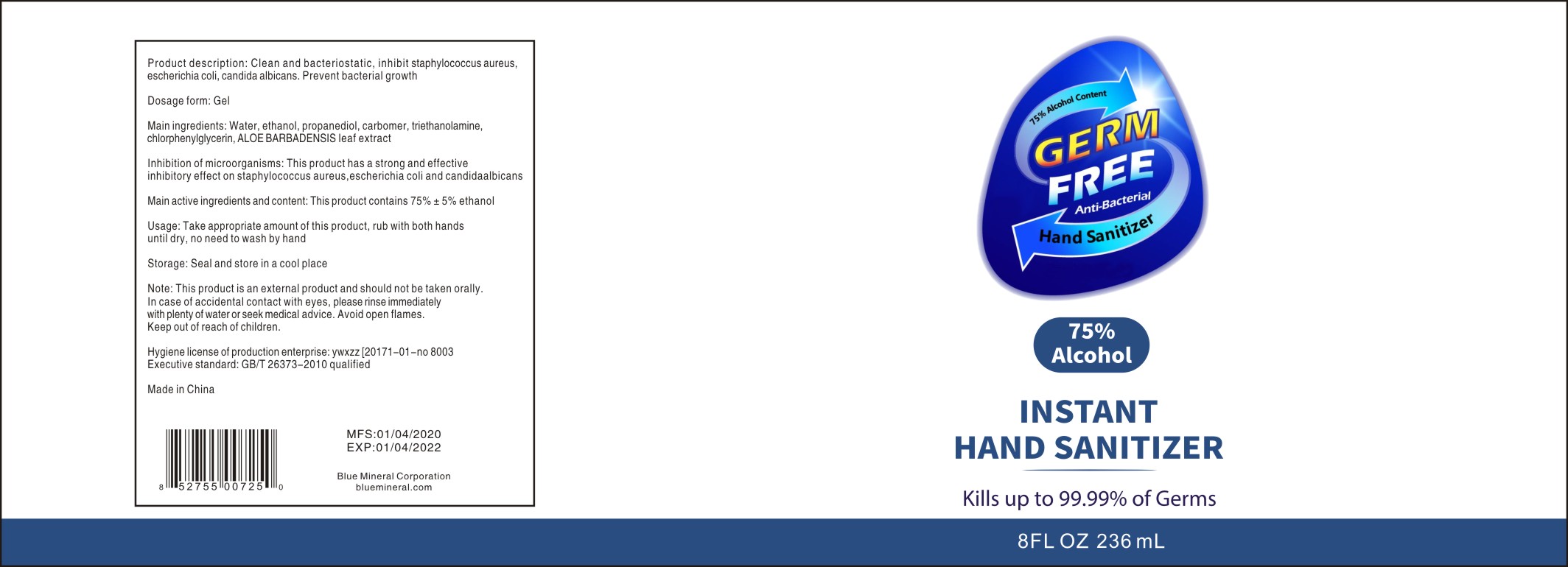 DRUG LABEL: GERM FREE Instant hand sanitizer
NDC: 77311-236 | Form: GEL
Manufacturer: Guangzhou Mengfeishi Pharmaceutical Technology Co., Ltd.
Category: otc | Type: HUMAN OTC DRUG LABEL
Date: 20200521

ACTIVE INGREDIENTS: ALCOHOL 75 mL/100 mL
INACTIVE INGREDIENTS: PROPANEDIOL; CHLORPHENESIN; ALOE VERA LEAF; WATER; CARBOMER HOMOPOLYMER, UNSPECIFIED TYPE; TROLAMINE

Main active ingredients and content

This product contains 75% ± 5% ethanol

Product description

Clean and bacteriostatic, inhibit staphylococcus aureus, escherichia coli, candida albicans. Prevent bacterial growth

Inhibition of microorganisms

This product has a strong and effective inhibitory effect on staphylococcus aureus, escherichia coli and candida albicans

Dosage form

Gel

Usage

Take appropriate amount of this prouct, rub with both hands until dry, no need to wash by hand

Note

This product is an external product and should not be taken orally. In case of accidental contact with eyes, please rinse immediately with plenty of water or seek medical advice. Avoid open flames.

Keep out of reach of children.

Main ingredients

Water, ethanol, propanediol, carbomer, triethanolamine, chlorphenylglycerin, ALOE BARBADENSIS leaf extract

Storage

Seal and store in a cool place